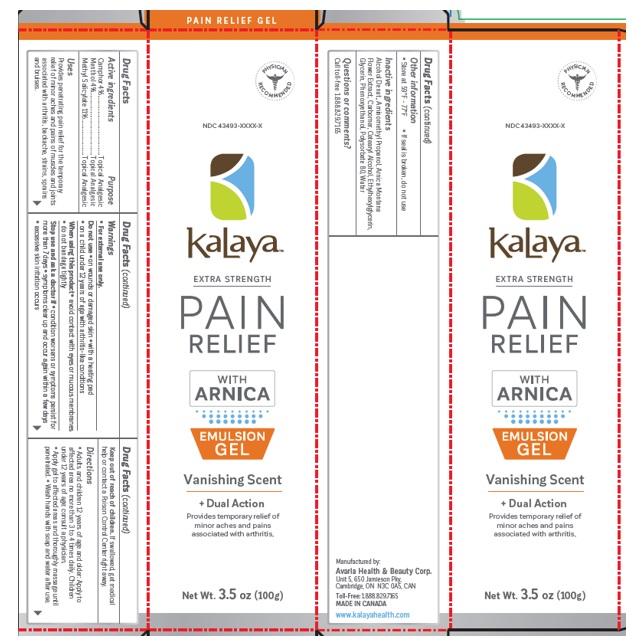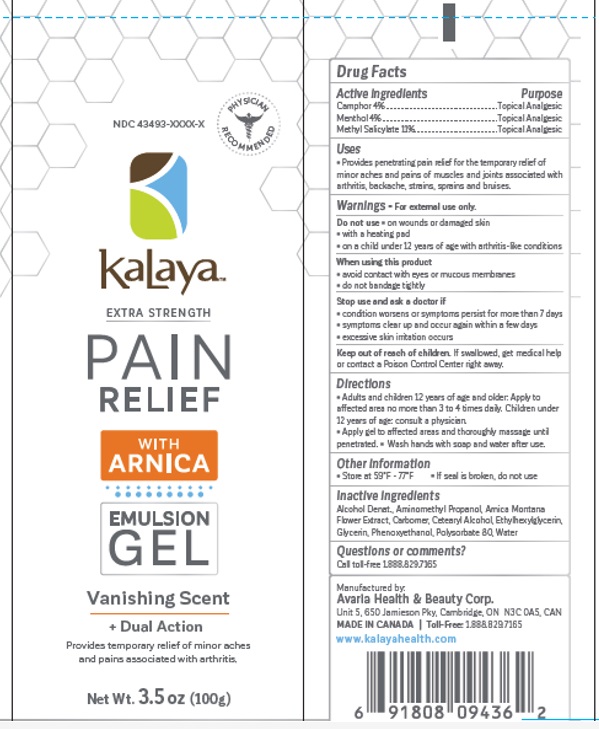 DRUG LABEL: Kalaya Extra Strength Pain Relief Gel with Arnica
NDC: 43493-0012 | Form: GEL
Manufacturer: Avaria Health & Beauty Corp
Category: otc | Type: HUMAN OTC DRUG LABEL
Date: 20251008

ACTIVE INGREDIENTS: METHYL SALICYLATE 11 g/100 g; LEVOMENTHOL 4 g/100 g; CAMPHOR (SYNTHETIC) 4 g/100 g
INACTIVE INGREDIENTS: ALCOHOL; AMINOMETHYLPROPANOL; ARNICA MONTANA FLOWER; CARBOMER INTERPOLYMER TYPE A (ALLYL SUCROSE CROSSLINKED); CETOSTEARYL ALCOHOL; ETHYLHEXYLGLYCERIN; PHENOXYETHANOL; GLYCERIN; POLYSORBATE 80; WATER

Active ingredients

Camphor 4%
Menthol 4%
Methyl salicylate 11%

Purpose

Topical Analgesic

Uses

Penetrating pain relief for the temporary relief of minor aches and pains of muscle and joint pain associated with arthritis, backache, strains, sprains and bruises.

Warnings

For external use only

Do not use

- on wounds or damaged skin
- with a heating pad
- on children under 12 years of age with arthritis-like conditions

When using this product

- avoid contact with eyes or mucous membranes
- do not bandage tightly

Stop use and ask a doctor

- condition worsen or symptoms persist for more than 7 days
- symptoms clear up and occur again within a few days
- excessive skin irritation occurs

Keep out of reach of children.

If swallowed, get medical help or contact a Poison Cntrol Center right away.

Directions

Adults and children 12 years and over. Use no more than 3-4 times daily. Apply cream to affected areas and thoroughly massage until penetrated. Wash hands with soap and water after use.

Other information

• Store at 59°F - 77°F

• If seal is broken, do not use

Inactive ingredients

Alcohol Denat., Aminomethyl propanol, Arnica Montana Flower Extract, Carbopol Ultrez 10, Cetearyl Alcohol, Ethylhexylglycerin, Phenoxyethanol, Glycerin, Polysorbate 80, Water

Questions or comments?

Call toll-free 1.888.829.7165